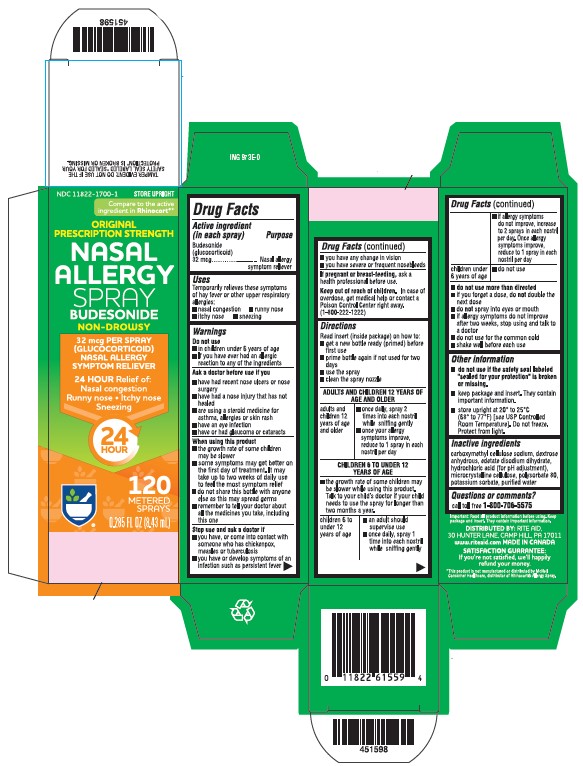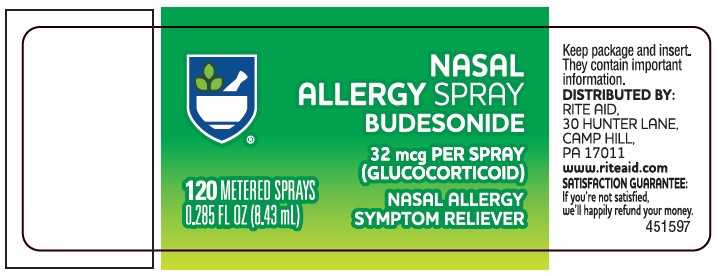 DRUG LABEL: Budesonide
NDC: 11822-1700 | Form: SPRAY, METERED
Manufacturer: Rite Aid Corporation
Category: otc | Type: HUMAN OTC DRUG LABEL
Date: 20251230

ACTIVE INGREDIENTS: BUDESONIDE 32 ug/1 1
INACTIVE INGREDIENTS: EDETATE DISODIUM; CARBOXYMETHYLCELLULOSE SODIUM, UNSPECIFIED; MICROCRYSTALLINE CELLULOSE; DEXTROSE, UNSPECIFIED FORM; POTASSIUM SORBATE; POLYSORBATE 80; HYDROCHLORIC ACID; WATER

Drug Facts

Active ingredient (in each spray)

Budesonide (glucocorticoid) 32 mcg

Purpose

Nasal allergy symptom reliever

Uses

Temporarily relieves these symptoms of hay fever or other upper respiratory allergies:

• nasal congestion • runny nose • itchy nose • sneezing

Warnings

Do not use

- in children under 6 years of age
- if you have ever had an allergic reaction to any of the ingredients

Ask a doctor before use if you

- have had recent nose ulcers or nose surgery
- have had a nose injury that has not healed
- are using a steroid medicine for asthma, allergies or skin rash
- have an eye infection
- have or had glaucoma or cataracts

When using this product

- the growth rate of some children may be slower
- some symptoms may get better on the first day of treatment. It may take up to two weeks of daily use to feel the most symptom relief.
- do not share this bottle with anyone else as this may spread germs
- remember to tell your doctor about all the medicines you take, including this one

Stop use and ask a doctor if

- you have, or come into contact with someone who has, chickenpox, measles or tuberculosis
- you have or develop symptoms of an infection such as persistent fever
- you have any change in vision
- you have severe or frequent nosebleeds

PREGNANCY OR BREAST FEEDING

If pregnant or breast-feeding, ask a health professional before use.

Keep out of reach of children.

In case of overdose, get medical help or contact a Poison Control Center right away (1-800-222-1222).

Direction

Read insert (inside package) on how to:

- get a new bottle ready (primed) before first use
- prime bottle again if not used for two days
- use the spray
- clean the spray nozzle

Other information

- do not use if the safety seal labeled "sealed for your protection" is broken or missing.
- keep package and insert. They contain important information.
- store at 20° to 25°C (68° to 77°F) [see USP Controlled Room Temperature]. Do not freeze. Protect from light.

Inactive ingredients

carboxymethyl cellulose sodium, dextrose anhydrous, edetate disodium dihydrate, hydrochloric acid (for pH adjustment), microcrystalline cellulose, polysorbate 80, potassium sorbate, purified water

Questions or comments?

call toll free 1-800-706-5575

Principal Display Panel - Carton

CARTON LABEL - PRINCIPAL DISPLAY PANEL - 32 mcg per spray

Rite Aid

Budesonide Nasal Spray

Allergy Spray

120 sprays

Relief of:

- Nasal Congestion
- Runny Nose
- Itchy Nose
- Sneezing

Principal Display Panel - Bottle

BOTTLE LABEL - PRINCIPAL DISPLAY PANEL - 32 mcg per spray

Rite Aid

Budesonide Nasal Spray

Allergy Spray

120 sprays